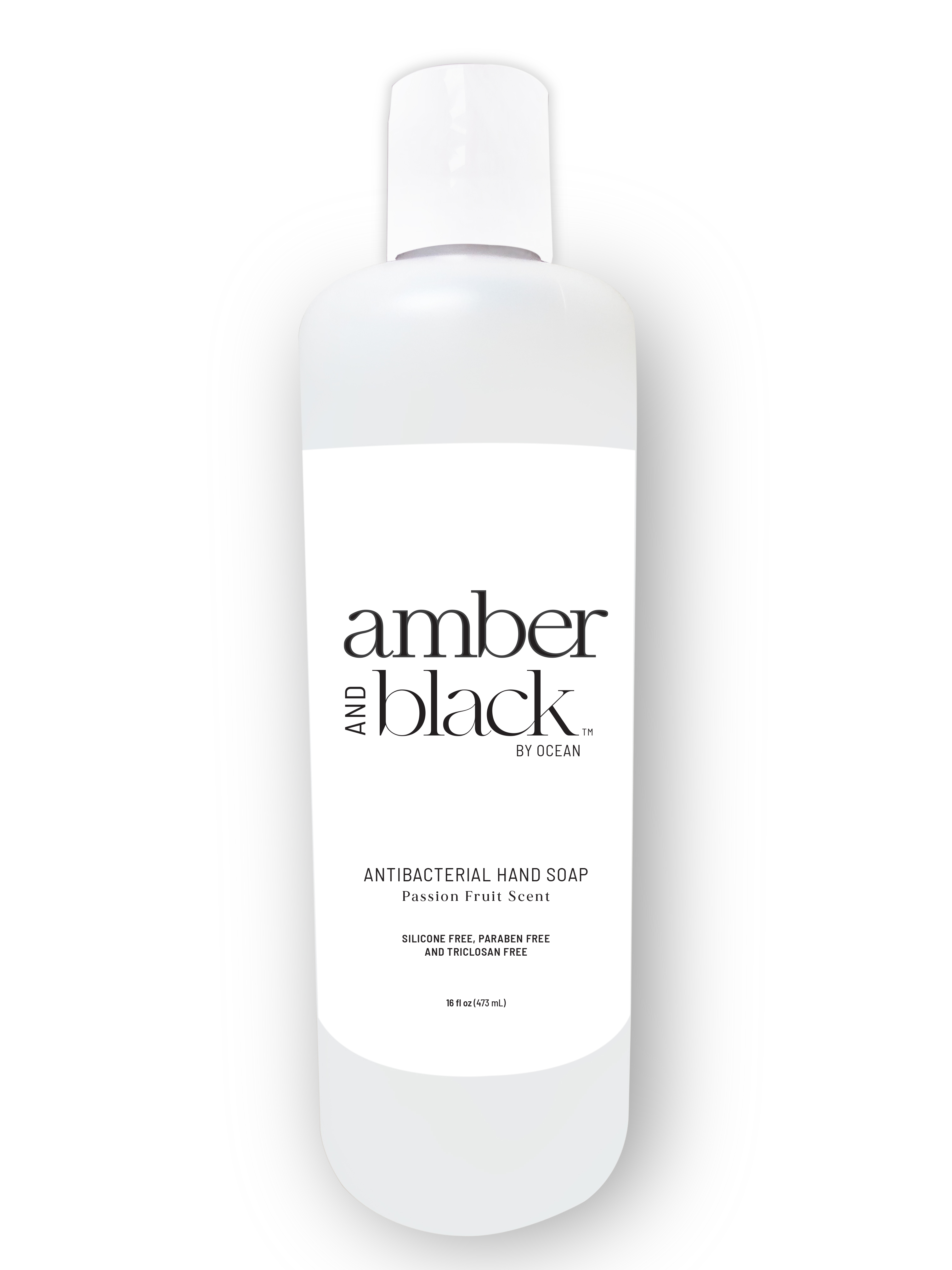 DRUG LABEL: Amber and Black
NDC: 73696-104 | Form: SOAP
Manufacturer: NV Labs
Category: otc | Type: HUMAN OTC DRUG LABEL
Date: 20220113

ACTIVE INGREDIENTS: BENZALKONIUM CHLORIDE 0.13 g/100 g
INACTIVE INGREDIENTS: PEG-150 DISTEARATE 0.3 g/100 g; FD&C RED NO. 40 2.15 g/100 g; MYRISTAMINE OXIDE 3.8 g/100 g; GLYCERIN 0.5 g/100 g; LAURAMIDOPROPYLAMINE OXIDE 4 g/100 g; SODIUM CHLORIDE 1.2 g/100 g; WATER 68.4896 g/100 g; COCAMIDOPROPYL BETAINE 9 g/100 g; CETRIMONIUM CHLORIDE 0.1 g/100 g; FD&C YELLOW NO. 5 1.4483 g/100 g; DITETRACYCLINE TETRASODIUM EDETATE 0.05 g/100 g; SODIUM BENZOATE 0.1 g/100 g; LAURAMINE OXIDE 11 g/100 g; D&C RED NO. 33 0.33 g/100 g; PEG-120 METHYL GLUCOSE DIOLEATE 0.1 g/100 g; ANHYDROUS CITRIC ACID 1 g/100 g

Amber and Black Antibacterial Hand Soap (16 Fl. Oz .)

Active Ingredient

Active Ingredient Purpose

Benzalkonium Chloride 0.13% v Antibacterial

USES

For handwashing to decrease bacteria of the skin

WARNING

Warnings

For External Use only

When using this product

Avoid Contact with eyes

In case of contact, rinse eyes thoroughly with water.

Stop use and ask a doctor if irritation orredness develops.

Keep out of reach of children, If swallowed, get medical help or contact a Poison Control Center right away.

Directions

- Apply to Dry Hands
- Lather vigorously for at least 15 seconds
- Rinse and dry throughly

In active Ingredients

Water (Aqua) , Lauramidopopylamine Oxide, cocamidopropyl Betaine, lauramine Oxide, Sodium Chloride, Glycerin, Myristamine Oxide, Cetrimonium Chloride, Fragrance, PEG-120 Methy Glucose Dioleate, PEG-150 Distearate, Citric Acid, Tetrasodium EDTA, Sodium Benzoate, RED 40, Red 33, Yellow 5.

Manufactured By: Questions or Comments

Manufactured By: Reforma Group, Southfield, Michigan 48033

Questions or comments? Call 1-248-358-9022

Keep out of Reach of Children. If swallowed , get medical help or contact a Poison Control Center right away.

Purpose

Antbacterial